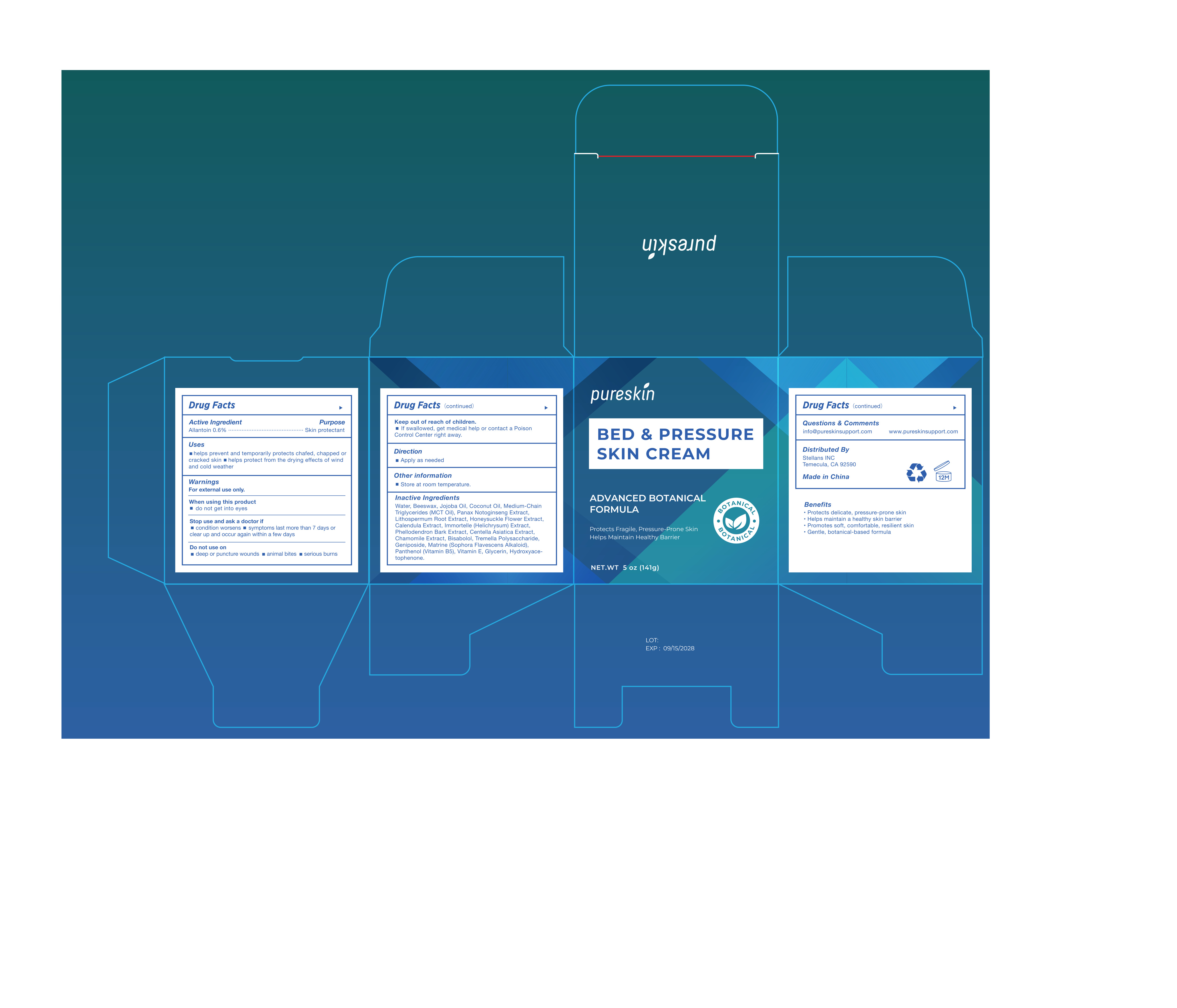 DRUG LABEL: Pureskin Bed and Pressure Sore
NDC: 87217-001 | Form: CREAM
Manufacturer: BENLONG HALL LLC
Category: otc | Type: HUMAN OTC DRUG LABEL
Date: 20251216

ACTIVE INGREDIENTS: ALLANTOIN 0.6 g/100 g
INACTIVE INGREDIENTS: LITHOSPERMUM ERYTHRORHIZON ROOT; CALENDULA OFFICINALIS FLOWER; .ALPHA.-BISABOLOL, (+/-)-; TREMELLA FUCIFORMIS WHOLE; GENIPOSIDE; LONICERA JAPONICA FLOWER; MATRINE; HELICHRYSUM ITALICUM FLOWER; MATRICARIA CHAMOMILLA WHOLE; PHELLODENDRON AMURENSE BARK; CENTELLA ASIATICA TRITERPENOIDS; GLYCERIN; WATER; PANAX NOTOGINSENG ROOT; HYDROXYACETOPHENONE; BEESWAX; MEDIUM-CHAIN TRIGLYCERIDES; JOJOBA OIL; COCONUT OIL; PANTHENOL; TOCOPHEROL

Drug Facts

Active ingredient

Allantoin 0.6%

Purpose

Skin protectant

Uses

- helps prevent and temporarily protects chafed, chapped or cracked skin
- helps protect from the drying effects of wind and cold weather

Warnings

For external use only.

When using this product

do not get into eyes

Stop use and ask a doctor if

- condition worsens
- symptoms last more than 7 days or clear up and occur again within a few days

Do not use on

- deep or puncture wounds
- animal bites
- serious burns

Keep out of reach of children.

If swallowed, get medical help or contact a Poison Control Center right away.

Directions

apply as needed

Other information

store at room temperature

Inactive ingredients

Water, Beeswax, Jojoba Oil, Coconut Oil, Medium-Chain Triglycerides (MCT Oil), Panax Notoginseng Extract (Panax Notoginseng Root), Lithospermum Root Extract (Lithospermum Erythrorhizon Root), Honeysuckle Flower Extract (Lonicera Japonica Flower), Calendula Extract (Calendula Officinalis Flower), Immortelle (Helichrysum) Extract (Helichrysum Italicum Flower), Phellodendron Bark Extract (Phellodendron Amurense Bark), Centella Asiatica Extract (Centella Asiatica Triterpenoids), Chamomile Extract (Matricaria Chamomilla Whole), Bisabolol (Alpha-Bisabolol (+/-)), Tremella Polysaccharide (Tremella Fuciformis Whole), Geniposide, Matrine (Sophora Flavescens Alkaloid), Panthenol (Vitamin B5), Vitamin E (Tocopherol), Glycerin, Hydroxyacetophenone.